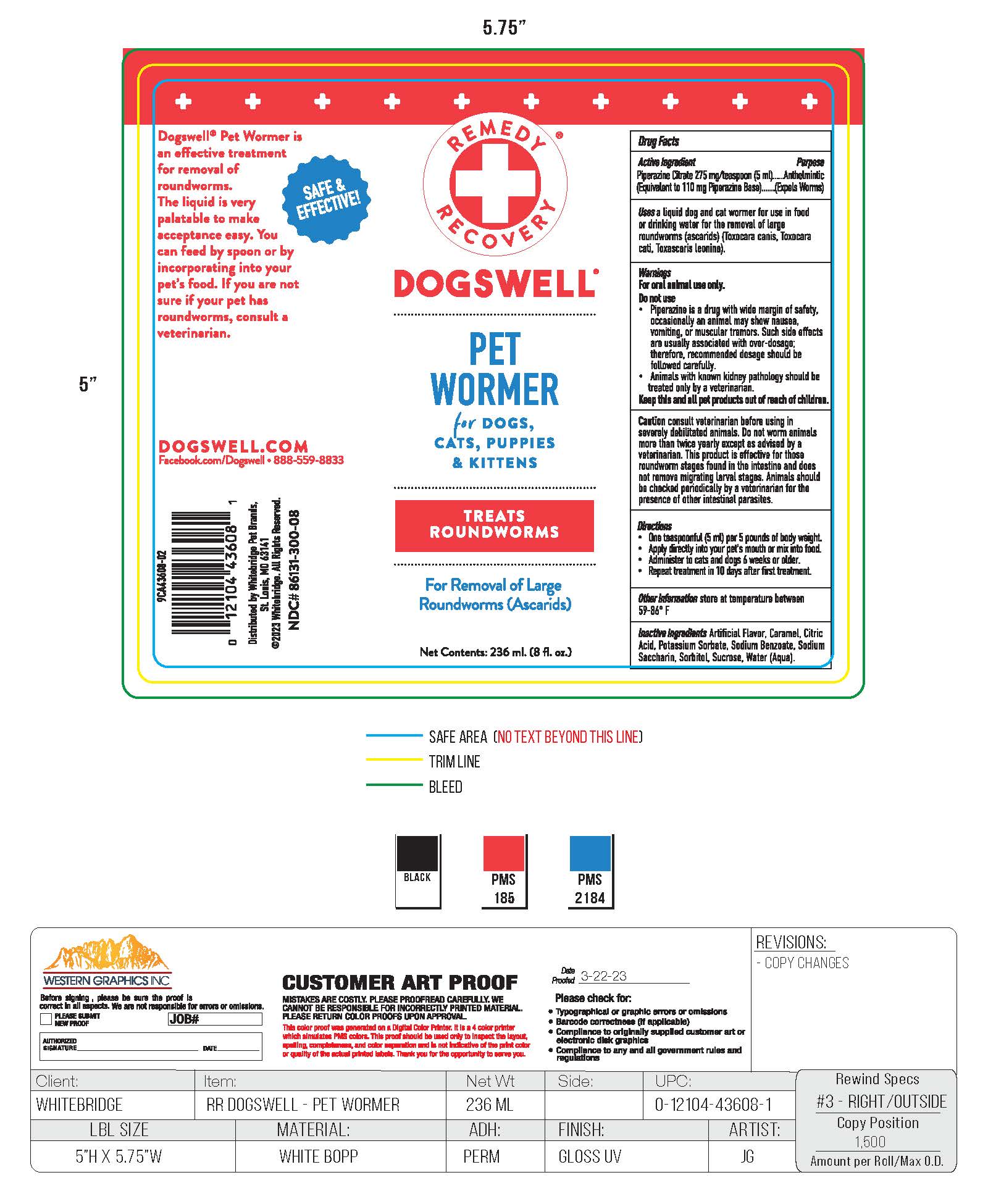 DRUG LABEL: WORMICIDE
NDC: 86131-300 | Form: SYRUP
Manufacturer: Whitebridge Pet Brands
Category: animal | Type: OTC ANIMAL DRUG LABEL
Date: 20251223

ACTIVE INGREDIENTS: PIPERAZINE CITRATE 5.5 g/100 mL
INACTIVE INGREDIENTS: WATER; SUCROSE; SORBITOL; SACCHARIN SODIUM; CARAMEL; CITRIC ACID MONOHYDRATE; POTASSIUM SORBATE; SODIUM BENZOATE

PET WORMER

DRUG FACTS

Active Ingredients

Piperazine Citrate 275 mg/teaspoon (5ml)

(Equivalent to 110 mg Piperazine Base)

Purpose

Anthelmintic

(Expels Worms)

Uses

a liquid dog and cat wormer for use in food or drinking water for the removal of large roundworms (ascarids) (Toxocara canis, Toxocara cati, Toxascaris leonina).

Warnings

For oral animal use only.

Do not use

- Piperazine is a drug with wide margin of safety, occasionally an animal may show nausea, vomiting, or muscular tremors. Such side effects are usually associated with over-dosage; therefore, recommended dosage should be followed carefully.
- Animals with known kidney pathology should be treated only by a veterinarian.

Keep this and all pet products out of reach of childern.

Caution

consult veterinarian before using in severely debilitated animals. Do not worm animals more than twice yearly except as advised by a veterinarian. This product is effective for those roundworm stages found in the intestine and does not remove migrating larval stages. Animals should be checked periodically by a veterinarian for the presence of other intestinal parasites.

Directions

- One teaspoonful (5 ml) per 5 pounds of body weight.
- Apply directly into infested animal mouth or mix into food, milk or water.
- Administer to cats and dogs 6 weeks or older.
- Repeat treatment in 10 days after first treatment

Other information

store at temperature between 59-86 F

Inactive ingredients

Artificial Flavor, Caramel, Citric Acid, Potassium Sorbate, Sodium Benzoate, Sodium Saccharin, Sorbitol, Sucrose, Water (Aqua).

DESCRIPTION

Dogswell Pet Wormer is an effective treatment for removal of roundworms. The liquid is very palatable to make acceptance easy. You can feed by spoon or by incorporating into your pet's water or food. If you are not sure if your pet has roundworms, consult a veterinarian.

DOGSWELL.COM

Facebook.com/Dogswell 888-559-8833

Distributed by Whitebridge Pet Brands,

St. Louis, MO 63141

2020 Whitebridge. All Rights Reserved.

NDC# 86131-300-08

PACKAGE LABEL

REMEDY RECOVERY

DOGSWELL

PET WORMER

for DOGS, CATS, PUPPIES & KITTENS

TREATS ROUNDWORMS

For Removal of Large Roundworms (Ascarids)

Net Contents: 236 ml. (8 fl. oz.)